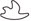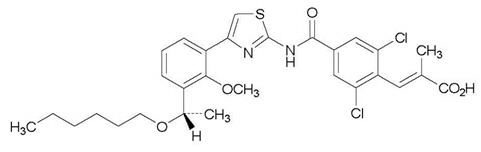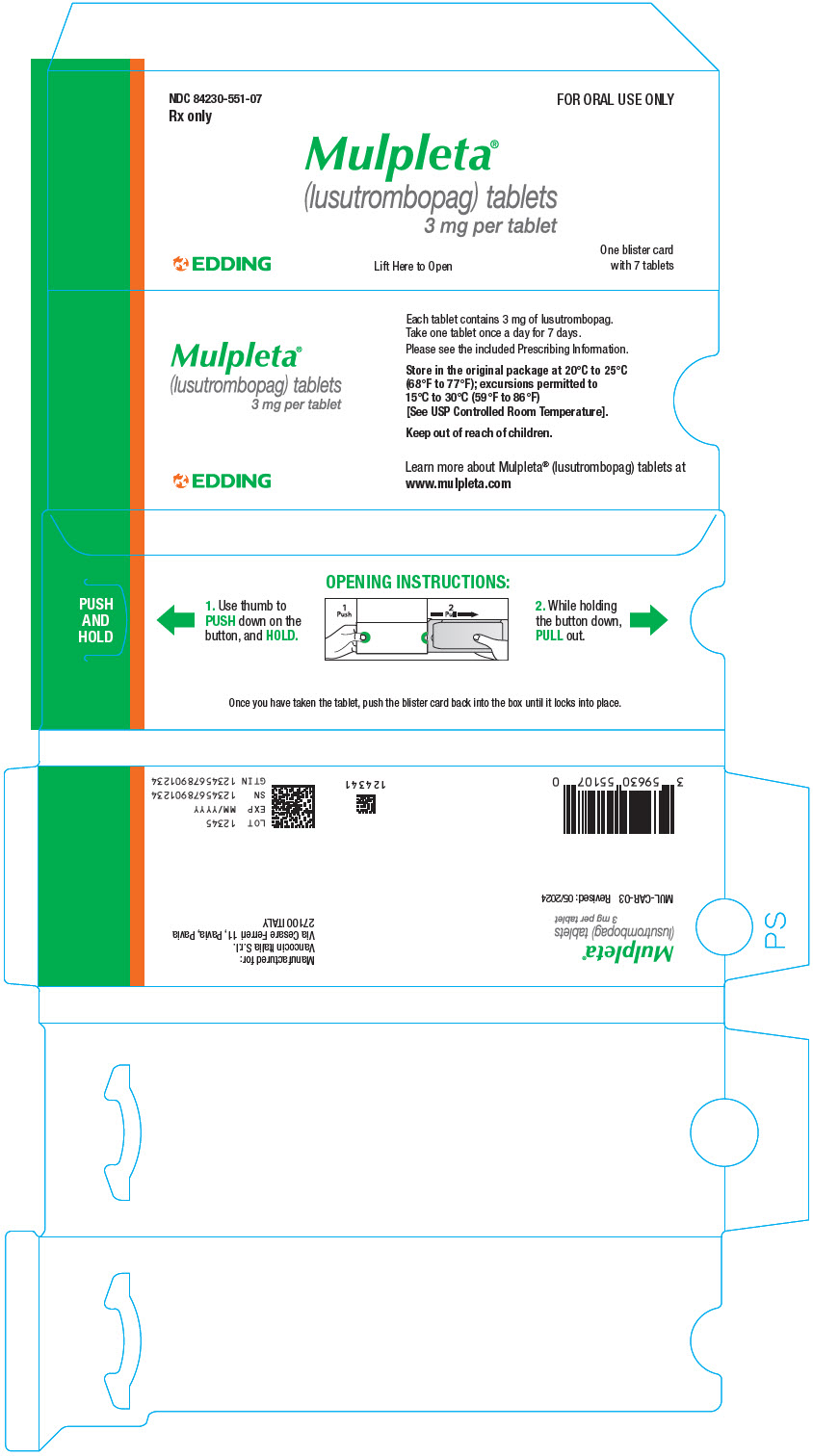 DRUG LABEL: Mulpleta
NDC: 84230-551 | Form: TABLET, FILM COATED
Manufacturer: VANCOCIN ITALIA SRL
Category: prescription | Type: HUMAN PRESCRIPTION DRUG LABEL
Date: 20251209

ACTIVE INGREDIENTS: LUSUTROMBOPAG 3 mg/1 1
INACTIVE INGREDIENTS: MICROCRYSTALLINE CELLULOSE; MAGNESIUM OXIDE; SODIUM LAURYL SULFATE; HYDROXYPROPYL CELLULOSE, UNSPECIFIED; CARBOXYMETHYLCELLULOSE CALCIUM; MAGNESIUM STEARATE; HYPROMELLOSE, UNSPECIFIED; TRIETHYL CITRATE; TITANIUM DIOXIDE; FERRIC OXIDE RED; TALC; MANNITOL

HIGHLIGHTS OF PRESCRIBING INFORMATION

These highlights do not include all the information needed to use MULPLETA safely and effectively. See full prescribing information for MULPLETA.
MULPLETA®(lusutrombopag tablets) for oral use
Initial U.S. Approval: 2018

1 INDICATIONS AND USAGE

MULPLETA is a thrombopoietin receptor agonist indicated for the treatment of thrombocytopenia in adult patients with chronic liver disease who are scheduled to undergo a procedure. (1)

2 DOSAGE AND ADMINISTRATION

- Begin MULPLETA dosing 8-14 days prior to a scheduled procedure. (2.1)
- Patients should undergo their procedure 2-8 days after the last dose. (2.1)
- Recommended Dosage: 3 mg orally once daily with or without food for 7 days. (2.1)

3 DOSAGE FORMS AND STRENGTHS

Tablet: 3 mg. (3)

4 CONTRAINDICATIONS

- None.

5 WARNINGS AND PRECAUTIONS

- Thrombotic/Thromboembolic Complications: MULPLETA is a thrombopoietin (TPO) receptor agonist, and TPO receptor agonists have been associated with thrombotic and thromboembolic complications in patients with chronic liver disease. Monitor platelet counts and for thromboembolic events and institute treatment promptly. (5.1)

6 ADVERSE REACTIONS

The most common adverse reaction (≥3%): headache. (6.1)

To report SUSPECTED ADVERSE REACTIONS, contact Shionogi Inc. at 1-800-849-9707 or FDA at 1-800-FDA-1088 or www.fda.gov/medwatch.

8 USE IN SPECIFIC POPULATIONS

- Lactation: Breastfeeding is not recommended during treatment. (8.2)

FULL PRESCRIBING INFORMATION

1 INDICATIONS AND USAGE

MULPLETA is indicated for the treatment of thrombocytopenia in adult patients with chronic liver disease who are scheduled to undergo a procedure.

2 DOSAGE AND ADMINISTRATION

2.1 Recommended Dosage

Begin MULPLETA dosing 8-14 days prior to a scheduled procedure.

Patients should undergo their procedure 2-8 days after the last dose.

The recommended dosage of MULPLETA is 3 mg taken orally once daily with or without food for 7 days. In the case of a missed dose of MULPLETA, patients should take the missed dose as soon as possible on the same day and return to the normal schedule the following day.

MULPLETA has been investigated only as a single 7-day once daily dosing regimen in clinical trials in patients with chronic liver disease [see Clinical Studies (14)] . MULPLETA should not be administered to patients with chronic liver disease in an attempt to normalize platelet counts.

2.2 Monitoring

Obtain a platelet count prior to initiation of MULPLETA therapy and not more than 2 days before the procedure.

3 DOSAGE FORMS AND STRENGTHS

Tablets: 3 mg lusutrombopag as a light red, round, film-coated tablet debossed with the Eddingpharm trademark () above the identifier code "551"on one side and with a "3" on the other side.

4 CONTRAINDICATIONS

None.

5 WARNINGS AND PRECAUTIONS

5.1 Thrombotic/Thromboembolic Complications

MULPLETA is a thrombopoietin (TPO) receptor agonist, and TPO receptor agonists have been associated with thrombotic and thromboembolic complications in patients with chronic liver disease. Portal vein thrombosis has been reported in patients with chronic liver disease treated with TPO receptor agonists. Portal vein thrombosis was reported in 1% (2 of 171) of MULPLETA-treated patients and 1% (2 of 170) of placebo-treated patients in 3 randomized, double-blind trials and was identified post-procedure in protocol-specified imaging. The thromboses were not associated with a marked increase in platelet count.

Consider the potential increased thrombotic risk when administering MULPLETA to patients with known risk factors for thromboembolism, including genetic pro-thrombotic conditions (Factor V Leiden, Prothrombin 20210A, Antithrombin deficiency, or Protein C or S deficiency). In patients with ongoing or prior thrombosis or absence of hepatopetal blood flow, MULPLETA should only be used if the potential benefit to the patient justifies the potential risk.

MULPLETA should not be administered to patients with chronic liver disease in an attempt to normalize platelet counts.

6 ADVERSE REACTIONS

The following serious adverse reactions are discussed in detail in other sections of the labeling:

- Thrombotic/Thromboembolic Complications [see Warnings and Precautions (5.1)]

6.1 Clinical Trials Experience

Because clinical trials are conducted under widely varying conditions, adverse reaction rates observed in the clinical trials of a drug cannot be directly compared to rates in the clinical trials of another drug and may not reflect the rates observed in practice.

The safety of MULPLETA was evaluated in 3 randomized, double-blind, placebo-controlled trials, L-PLUS 1, L-PLUS 2, and M0626, in which patients with chronic liver disease and thrombocytopenia were treated with MULPLETA (N=171) or placebo (N=170) at a dose of 3 mg daily for up to 7 days prior to a scheduled procedure.

The majority of patients were males (59%), and median age was 61 years (range 19-88). The racial and ethnic distribution was White (50%), Asian (47%), Black (<1%), and Other (3%).

The most common adverse reactions (those occurring in at least 3%) in the MULPLETA-treated group across the pooled data from the three trials are summarized in table 1.

Table 1. Adverse Reactions with a Frequency ≥3% in Patients Treated with MULPLETA (Pooled Data (L-PLUS 1, L-PLUS 2, and M0626))
Adverse Reaction [Includes treatment-emergent adverse reactions occurring at a rate higher than placebo.] | MULPLETA 3 mg (N=171) % | Placebo (N=170) %
Headache | 5 | 4

The incidence of serious adverse events was 5% (9 of 171 patients) in the MULPLETA group and 7% (12 of 170 patients) in the placebo group. The most common serious adverse reaction reported with MULPLETA was portal vein thrombosis [see Warnings and Precautions (5.1)] . No adverse reactions resulted in discontinuation of MULPLETA.

8 USE IN SPECIFIC POPULATIONS

8.1 Pregnancy

Risk Summary

There are no available data on MULPLETA in pregnant women to inform the drug-associated risk. In animal reproduction studies, oral administration of lusutrombopag to pregnant rats during organogenesis and the lactation period resulted in adverse developmental outcomes. These findings were observed at exposures based on AUC that were substantially higher than the AUC observed in patients (approximately 89 times) at the recommended clinical dose of 3 mg once daily .Advise pregnant women of the potential risk to a fetus (see Data) .

The background risk of major birth defects and miscarriage for the indicated population is unknown. All pregnancies have a background risk of birth defect, loss, or other adverse outcomes. In the general population in the United States, the estimated background risk of major birth defects and miscarriage in clinically recognized pregnancies is 2% to 4% and 15% to 20%, respectively.

Data

Animal Data

In an embryo-fetal development study in rats, lusutrombopag was orally administered during organogenesis at doses of 4, 12.5, 40, and 80 mg/kg/day. Low body weight and a decrease in the number of ossified sternebrae were noted in fetuses at 80 mg/kg/day (approximately 251 times the AUC observed in patients at the recommended clinical dose of 3 mg once daily). Minor skeletal variations (supernumerary ribs) were observed at doses of 4 mg/kg/day (approximately 23 times the AUC observed in patients at the recommended clinical dose of 3 mg once daily).

In an embryo-fetal development study in rabbits following oral administration of lusutrombopag at doses up to 1000 mg/kg/day, no effect of lusutrombopag was observed on any parameter of embryo-fetal development.

In a pre- and postnatal development study in rats at oral doses of 1, 4, 12.5, and 40 mg/kg/day, there were adverse effects of lusutrombopag on postnatal development at 40 mg/kg/day (approximately 230 times the AUC observed in patients at the recommended clinical dose of 3 mg once daily). The effects included prolongation of the gestation period in dams, low viability before weaning, delayed postnatal growth (delayed negative geotaxis, delayed eyelid opening, or low pup body weight), abnormal clinical signs (prominent annular rings on the tail after weaning), low fertility index, a low number of corpora lutea or implantations, and increased pre-implantation loss. The incidence of short thoracolumbar supernumerary ribs on postnatal Day 4 of F1 pups was high at doses of 12.5 mg/kg/day or more (approximately 89 times the AUC observed in patients at the recommended clinical dose of 3 mg once daily).

8.2 Lactation

Risk Summary

There is no information regarding the presence of lusutrombopag in human milk, the effects on the breastfed child, and the effects on milk production. Lusutrombopag was present in the milk of lactating rats. Due to the potential for serious adverse reactions in a breastfed child, breastfeeding is not recommended during treatment with MULPLETA and for at least 28 days after the last dose (see Clinical Considerations) .

Clinical Considerations

Minimizing Exposure

A lactating woman should interrupt breastfeeding and pump and discard breast milk during MULPLETA treatment and for 28 days after the last dose of MULPLETA in order to minimize exposure to a breastfed child.

8.4 Pediatric Use

Safety and effectiveness in pediatric patients have not been established.

8.5 Geriatric Use

Clinical studies of MULPLETA did not include sufficient numbers of subjects aged 65 and over to determine whether they respond differently from younger subjects. Other reported clinical experience has not identified differences in responses between the elderly and younger patients.

10 OVERDOSAGE

No antidote for MULPLETA overdose is known.

In the event of overdose, platelet count may increase excessively and result in thrombotic or thromboembolic complications. Closely monitor the patient and platelet count. Treat thrombotic complications in accordance with standard of care.

Hemodialysis is not expected to enhance the elimination of MULPLETA because lusutrombopag is highly bound to protein in plasma [see Clinical Pharmacology (12.3)] .

11 DESCRIPTION

MULPLETA (lusutrombopag), a thrombopoietin (TPO) receptor agonist, contains lusutrombopag as the active ingredient.

The chemical name for lusutrombopag is (2 E)-3-{2,6-Dichloro-4-[(4-{3-[(1 S)-1-(hexyloxy) ethyl]-2-methoxyphenyl}-1,3-thiazol-2-yl) carbamoyl]phenyl}-2-methylprop-2-enoic acid.

The structural formula is:

The empirical formula for lusutrombopag is C29H32Cl2N2O5S and the molecular weight is 591.54.

Lusutrombopag is a white to slightly yellowish white powder, and is freely soluble in N,N-dimethylformamide, slightly soluble in ethanol (99.5%) and methanol, very slightly soluble in acetonitrile, and practically insoluble in water. Lusutrombopag is slightly soluble in the buffer solution at pH 11 and practically insoluble in buffer solutions with pH ranges of 1 to 9.

MULPLETA (lusutrombopag) tablets for oral use contain lusutrombopag 3 mg.

Excipients are D-mannitol, microcrystalline cellulose, magnesium oxide, sodium lauryl sulfate, hydroxypropyl cellulose, carboxymethylcellulose calcium, magnesium stearate, hypromellose, triethyl citrate, titanium dioxide, red ferric oxide, and talc.

12 CLINICAL PHARMACOLOGY

12.1 Mechanism of Action

Lusutrombopag is an orally bioavailable, small molecule TPO receptor agonist that interacts with the transmembrane domain of human TPO receptors expressed on megakaryocytes to induce the proliferation and differentiation of megakaryocytic progenitor cells from hematopoietic stem cells and megakaryocyte maturation.

12.2 Pharmacodynamics

Platelet Response

Lusutrombopag upregulates the production of platelets through its agonistic effect on human TPO receptors.

The effect of lusutrombopag on platelet count increase was correlated with the AUC across the studied dose range of 0.25 mg to 4 mg in thrombocytopenic patients with chronic liver disease. With the 3 mg daily dose, the mean (standard deviation) maximum platelet count in patients (N=74) without platelet transfusion was 86.9 (27.2) × 10^9/L, and the median time to reach the maximum platelet count was 12.0 (5 to 35) days.

Cardiac Electrophysiology

At a dose 8 times the recommended dosage, MULPLETA does not prolong QT interval to any clinically relevant extent.

12.3 Pharmacokinetics

Lusutrombopag demonstrated dose-proportional pharmacokinetics after single doses ranging from 1 mg (0.33 times the lowest approved dosage) to 50 mg (16.7 times the highest recommended dosage). Healthy subjects administered 3 mg of lusutrombopag had a geometric mean (%CV) maximal concentration (Cmax) of 111 (20.4) ng/mL and area under the time-concentration curve extrapolated to infinity (AUC0-inf) of 2931 (23.4) ng.hr/mL. The pharmacokinetics of lusutrombopag were similar in both healthy subjects and the chronic liver disease population.

The accumulation ratios of Cmaxand AUC were approximately 2 with once-daily multiple-dose administration, and steady-state plasma lusutrombopag concentrations were achieved after Day 5.

Absorption

In patients with chronic liver disease, the time to peak lusutrombopag concentration (Tmax) was observed 6 to 8 hours after oral administration.

Food Effect

Lusutrombopag AUC and Cmaxwere not affected when MULPLETA was co-administered with a high-fat meal (a total of approximately 900 calories, with 500, 250, and 150 calories from fat, carbohydrate, and protein, respectively) .

Distribution

The mean (%CV) lusutrombopag apparent volume of distribution in healthy adult subjects was 39.5 (23.5) L. The plasma protein binding of lusutrombopag is more than 99.9%.

Elimination

The terminal elimination half-life (t1/2) in healthy adult subjects was approximately 27 hours. The mean (%CV) clearance of lusutrombopag in patients with chronic liver disease is estimated to be 1.1 (36.1) L/hr.

Metabolism

Lusutrombopag is primarily metabolized by CYP4 enzymes, including CYP4A11.

Excretion

Fecal excretion accounted for 83% of the administered dose, with 16% of the dose excreted as unchanged lusutrombopag, and urinary excretion accounted for approximately 1%.

Specific Populations

No clinically significant differences in the pharmacokinetics of lusutrombopag were observed based on age or race/ethnicity. Though lusutrombopag exposure tends to decrease with increasing body weight, differences in exposure are not considered clinically relevant.

Patients with Renal Impairment

A population pharmacokinetic analysis did not find a clinically meaningful effect of mild (creatinine clearance (CLcr) 60 to less than 90 mL/min) and moderate (CLcr 30 to less than 60 mL/min) renal impairment on the pharmacokinetics of lusutrombopag. Data in patients with severe renal impairment (CLcr less than 30 mL/min) are limited.

Patients with Hepatic Impairment

No clinically significant differences in the pharmacokinetics of lusutrombopag were observed based on mild to moderate (Child-Pugh class A and B) hepatic impairment.

The mean observed lusutrombopag Cmaxand AUC0-τdecreased by 20% to 30% in patients (N=5) with severe (Child-Pugh class C) hepatic impairment compared to patients with Child-Pugh class A and class B liver disease. However, the ranges for Cmaxand AUC0-τoverlapped among patients with Child-Pugh class A, B, and C liver disease.

Drug Interaction Studies

Clinical Studies

No clinically significant changes in lusutrombopag exposure were observed when co-administered with cyclosporine (an inhibitor of P-gp and BCRP) or an antacid containing a multivalent cation (calcium carbonate).

No clinically significant changes in midazolam (a CYP3A substrate) exposure were observed when co-administered with lusutrombopag.

In Vitro Studies

CYP Enzymes: lusutrombopag has low potential to inhibit CYP enzymes (CYP1A2, CYP2A6, CYP2B6, CYP2C8, CYP2C9, CYP2C19, CYP2D6, and CYP3A4/5). Lusutrombopag did not induce CYP1A2, CYP2C9, or CYP3A4.

UGT Enzymes: lusutrombopag did not induce UGT1A2, UGT1A6, or UGT2B7.

Transporter Systems: lusutrombopag is a substrate of P-gp and BCRP. Lusutrombopag has low potential to inhibit P-gp, BCRP, OATP1B1, OATP1B3, OCT1, OCT2, OAT1, OAT3, MATE1, MATE2-K, and BSEP.

13 NONCLINICAL TOXICOLOGY

13.1 Carcinogenesis, Mutagenesis, Impairment of Fertility

In 2-year studies, lusutrombopag was not carcinogenic to rats at oral doses up to 20 mg/kg/day in males and 2 mg/kg/day in females (a dose 49 times and 30 times, respectively, the human exposure (AUC) at the recommended clinical dose of 3 mg/day for 7 days) and to mice at oral doses up to 20 mg/kg/day in males and females (a dose approximately 45 times the human exposure (AUC) at the recommended clinical dose of 3 mg/day for 7 days).

Lusutrombopag was not genotoxic based on an in vitro bacterial reverse mutation (Ames) assay, a chromosomal aberration assay with cultured Chinese hamster lung cells, and an in vivo micronucleus assay with mouse bone marrow cells.

In a fertility and early embryonic development study, lusutrombopag did not affect fertility in male and female rats at oral doses up to 100 mg/kg/day (a dose in males and females approximately 176 and 252 times, respectively, the human exposure (AUC) at the recommended clinical dose of 3 mg/day for 7 days).

14 CLINICAL STUDIES

The efficacy of MULPLETA for the treatment of thrombocytopenia in patients with chronic liver disease who are scheduled to undergo a procedure was evaluated in 2 randomized, double-blind, placebo-controlled trials (L-PLUS 1 (N=97) and L-PLUS 2 (N=215; NCT02389621)). Patients with chronic liver disease who were undergoing an invasive procedure and had a platelet count less than 50 × 10^9/L were eligible to participate. Patients undergoing laparotomy, thoracotomy, open-heart surgery, craniotomy, or organ resection were excluded. Patients with a history of splenectomy, partial splenic embolization, or thrombosis and those with Child-Pugh class C liver disease, absence of hepatopetal blood flow, or a prothrombotic condition other than chronic liver disease were not allowed to participate.

The patient populations were similar between the MULPLETA and placebo arms and consisted of 60% male and 40% female; median age was 60 years (range 19-88). The racial and ethnic distribution was White (55%), Asian (41%), and Other (4%).

Patients were randomized 1:1 to receive 3 mg of MULPLETA or placebo once daily for up to 7 days. Randomization was stratified by liver ablation/coagulation or other procedures and the platelet count at screening/baseline. In L-PLUS 1, 57% of patients underwent procedures other than liver ablation/coagulation and 43% underwent liver ablation/coagulation (RFA/MCT). In L-PLUS 2, 98% of patients underwent procedures other than liver ablation/coagulation and 2% underwent liver ablation/coagulation (RFA/MCT). Procedures other than liver ablation/coagulation (RFA/MCT) included liver-related procedures (transcatheter arterial chemoembolization, liver biopsy, and others), upper and lower gastrointestinal endoscopy-related procedures (endoscopic variceal ligation, endoscopic injection sclerotherapy, polypectomy, and biopsy), and other procedures (dental extraction, diagnostic paracentesis or laparocentesis, septoplasty, embolization of splenic artery aneurysm, bone marrow biopsy, removal of cervical polyp, and inguinal hernia repair (non-laparotomy based)).

In L-PLUS 1, the major efficacy outcome was the proportion of patients who require no platelet transfusion prior to the primary invasive procedure. In L-PLUS 2, the major efficacy outcome was the proportion of patients who require no platelet transfusion prior to the primary invasive procedure and no rescue therapy for bleeding (i.e., platelet preparations, other blood preparations, including red blood cells and plasma, volume expanders) from randomization through 7 days after the primary invasive procedure. In both trials, additional efficacy outcomes included the proportion of patients who require no platelet transfusion during the study, proportion of responders, duration of the increase in platelet count defined as the number of days during which the platelet count was maintained as ≥50 × 10^9/L, and the time course of platelet counts.

In both the L-PLUS 1 and L-PLUS 2 trials, responders were defined as patients who had a platelet count of ≥50 × 10^9/L with an increase of ≥20 × 10^9/L from baseline.

Table 2. L-PLUS 1 Trial: Proportion of Patients Not Requiring Platelet Transfusion Prior to Invasive Procedure and Proportion of Responders
Endpoint | Proportion (n/N) Exact 95% Confidence Interval |  | Treatment Difference (95% Confidence Interval) p value
Endpoint | MULPLETA (N=49) | Placebo (N=48) | Treatment Difference (95% Confidence Interval) p value
Not requiring platelet transfusion prior to invasive procedure [A platelet transfusion was required if the platelet count was less than 50 × 10 9/L.] | 78% (38/49) (63, 88) | 13% (6/48) (4.7, 25) | 64 (49, 79) <0.0001 [Cochran-Mantel-Haenszel test with baseline platelet count as stratum; p value and confidence interval calculated using Wald method.]
Responder [Platelet count reached at least 50 × 10 9/L and increased at least 20 × 10 9/L from baseline.] during study | 76% (37/49) (61, 87) | 6% (3/48) (1.3, 17) | 68 (54, 82) <0.0001

Table 3. L-PLUS 2 Trial: Proportion of Patients Not Requiring Platelet Transfusion Prior to Invasive Procedure or Rescue Therapy for Bleeding Through 7 Days After Invasive Procedure and Proportion of Responders
Endpoint | Proportion (n/N) Exact 95% Confidence Interval |  | Treatment Difference (95% Confidence Interval) p value
Endpoint | MULPLETA (N=108) | Placebo (N=107) | Treatment Difference (95% Confidence Interval) p value
Not requiring platelet transfusion prior to invasive procedure [A platelet transfusion was required if the platelet count was less than 50 × 10 9/L.] or rescue therapy for bleeding from randomization through 7 days after invasive procedure | 65% (70/108) (55, 74) | 29% (31/107) (21, 39) | 37 (25, 49) <0.0001 [Cochran-Mantel-Haenszel test with baseline platelet count as stratum; p value and confidence interval calculated using Wald method.]
Responder [Platelet count reached at least 50 × 10 9/L and increased at least 20 × 10 9/L from baseline.] during study | 65% (70/108) (55, 74) | 13% (14/107) (7.3, 21) | 52 (41, 62) <0.0001

The median (Q1, Q3) duration of platelet count increase to at least 50 × 10^9/L was 22 (17, 27) days in MULPLETA-treated patients without platelet transfusion and 1.8 (0.0, 8.3) days in placebo-treated patients with platelet transfusion in L-PLUS 1 and 19 (13, 28) days in MULPLETA-treated patients without platelet transfusion and 0.0 (0.0, 5.0) days in placebo-treated patients with platelet transfusion in L-PLUS 2.

16 HOW SUPPLIED/STORAGE AND HANDLING

MULPLETA is supplied as 3 mg lusutrombopag tablets in a child-resistant blister pack containing 7 tablets - NDC 84230-551-07.

STORAGE AND HANDLING

Store MULPLETA in the original package at 20°C to 25°C (68°F to 77°F); excursions permitted to 15°C to 30°C (59°F to 86°F) [See USP Controlled Room Temperature].

17 PATIENT COUNSELING INFORMATION

Advise the patient to read the FDA-approved patient labeling (Patient Information).

Prior to treatment, patients should fully understand and be informed of the following risks and considerations for MULPLETA.

Risks

Thrombotic/Thromboembolic Complications

MULPLETA is a thrombopoietin (TPO) receptor agonist, and TPO receptor agonists have been associated with thrombotic and thromboembolic complications in patients with chronic liver disease. Portal vein thrombosis has been reported in patients with chronic liver disease treated with TPO receptor agonists.

Pregnancy

Advise women of reproductive potential who become pregnant or are planning to become pregnant that MULPLETA should be used during pregnancy only if the potential benefit to the mother justifies the potential risk to the fetus [see Use in Specific Populations (8.1)] .

Lactation

Advise women not to breastfeed during treatment with MULPLETA and for 28 days after the last dose of MULPLETA. Advise women to pump and discard breast milk during this period [see Use in Specific Populations (8.2)] .

MULPLETA is a registered trademark of Eddingpharm (Hong Kong) Company Limited

Manufactured for: Vancocin Italia S.r.l., Via Cesare Ferreri 11, Pavia,
Pavia 27100 ITALY

PATIENT INFORMATION
MULPLETA®(mul ple' tah)
(lusutrombopag)
Tablets

What is MULPLETA?

MULPLETA is a prescription medicine used to treat low platelet count (thrombocytopenia) in adults with chronic liver disease who are scheduled to have a procedure.

MULPLETA is not used to make platelet count normal in people with chronic liver disease.

It is not known if MULPLETA is safe and effective in children.

Before taking MULPLETA, tell your healthcare provider about all of your medical conditions,including if you:

- have a blood clot or have had a history of a blood clot.
- have any blood clotting problems, other than thrombocytopenia.
- are pregnant or plan to become pregnant. MULPLETA may harm your baby.
- are breastfeeding or plan to breastfeed. It is not known if MULPLETA passes into your breast milk. Do not breastfeed during your treatment with MULPLETA and for at least 28 days after your last dose. Talk to your healthcare provider about the best way to feed your baby during your treatment with MULPLETA.

Tell your healthcare provider about all the medicines you take,including prescription and over-the-counter medicines, vitamins, and herbal supplements.

How should I take MULPLETA?

- Take MULPLETA exactly as your healthcare provider tells you to take it.
- Your healthcare provider will tell you when to start taking MULPLETA.
- Take MULPLETA 1 time each day for 7 days.
- MULPLETA may be taken with or without food.
- If you miss a dose of MULPLETA, take the missed dose as soon as possible on the same day and return to your normal schedule the following day.
- If you take too much MULPLETA, call your healthcare provider or go to the nearest hospital emergency room right away.
- Your healthcare provider will check your platelet count before you start treatment with MULPLETA and before your procedure.

What are the possible side effects of MULPLETA?

MULPLETA may cause serious side effects,including:

Blood clots,including blood clots in the liver, may happen in people with chronic liver disease and who take MULPLETA. You may have an increased risk of blood clots if you have certain blood clotting conditions.

The most common side effect of MULPLETAis headache.

These are not all of the possible side effects of MULPLETA.

Call your doctor for medical advice about side effects. You may report side effects to FDA at 1-800-FDA-1088.

How should I store MULPLETA?

- Store MULPLETA at room temperature between 68°F and 77°F (20°C to 25°C).
- MULPLETA comes in a child-resistant blister pack. Keep MULPLETA in the packaging that it comes in.

Keep MULPLETA and all medicines out of the reach of children.

General information about the safe and effective use of MULPLETA.

Medicines are sometimes prescribed for purposes other than those listed in a Patient Information leaflet. Do not use MULPLETA for a condition for which it was not prescribed. Do not give MULPLETA to other people, even if they have the same symptoms that you have. It may harm them. You can ask your pharmacist or healthcare provider for information about MULPLETA that is written for healthcare professionals.

What are the ingredients of MULPLETA?

Active ingredient:lusutrombopag.

Inactive ingredients:D-mannitol, microcrystalline cellulose, magnesium oxide, sodium lauryl sulfate, hydroxypropyl cellulose, carboxymethylcellulose calcium, magnesium stearate, hypromellose, triethyl citrate, titanium dioxide, red ferric oxide, and talc.

Manufactured for: Vancocin Italia S.r.l., Via Cesare Ferreri 11, Pavia,
Pavia 27100 ITALY

For more information, go to www.mulpleta.comor call 1-800-849-9707.

This Patient Information has been approved by the U.S. Food and Drug Administration.

Revised: 02/2024

PRINCIPAL DISPLAY PANEL - 3 mg Tablet Blister Card Carton

NDC 84230-551-07
Rx only

FOR ORAL USE ONLY

Mulpleta®
(lusutrombopag) tablets
3 mg per tablet

EDDING

Lift Here to Open

One blister card
with 7 tablets